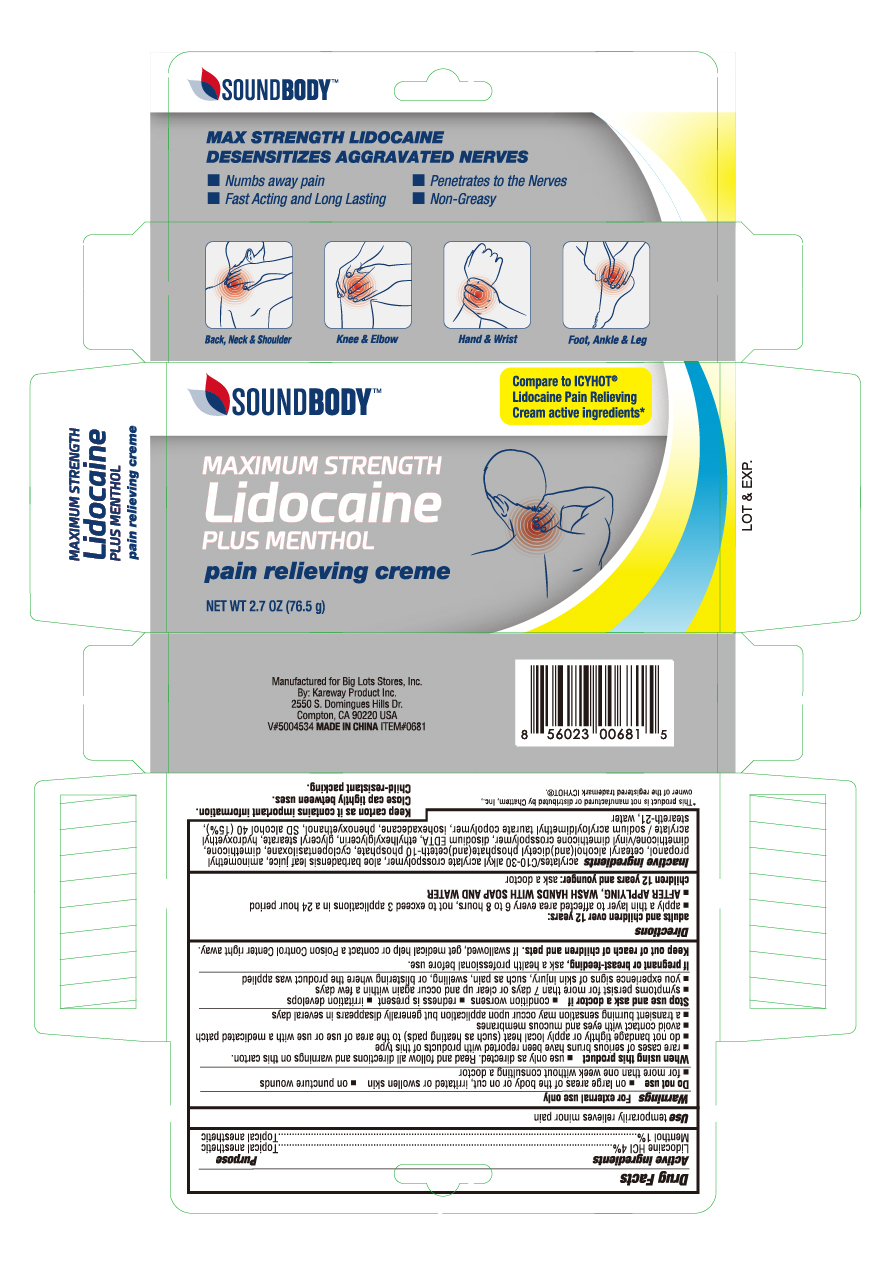 DRUG LABEL: Lidocaine with Menthol
NDC: 67510-0681 | Form: CREAM
Manufacturer: Kareway Product, Inc.
Category: otc | Type: HUMAN OTC DRUG LABEL
Date: 20250408

ACTIVE INGREDIENTS: LIDOCAINE 0.4 g/1 g; MENTHOL 0.1 g/1 g
INACTIVE INGREDIENTS: CARBOMER INTERPOLYMER TYPE A (55000 CPS); ALOE VERA LEAF; AMINOMETHYLPROPANOL; CAPRYLYL TRISILOXANE; CYCLOMETHICONE 5; DIMETHICONE/VINYL DIMETHICONE CROSSPOLYMER (SOFT PARTICLE); DIHEXADECYL PHOSPHATE; DIMETHICONE; EDETATE DISODIUM; ETHYLHEXYLGLYCERIN; GLYCERYL MONOSTEARATE; ISOHEXADECANE; POLYSORBATE 60; ALCOHOL; STEARETH-21; WATER

67510-0681

Active Ingredients

Lidocaine HCl 4%

Purposes

Topical anesthetic

Active Ingredients

Menthol 1 %

Purposes

Topical analgesic

Uses

Temporarily relieves minor pain

Warnings

For external use only

Do not use

- on large areas of the body or on cut, irritated or swollen skin
- on puncture wounds
- for more than one week without consulting a doctor

When using this product

- Use only as directed. Read and follow all directions and warnings on this label
- rare cases of serious burns have been reported with products of this type
- do not bandage tightly or apply local heat (such as heating pads) to the area of use or use with a medicated patch
- avoid contact with eyes and mucous membranes
- a transient burning sensation may occur upon application but generally disappears in several days

Stop use and ask a doctor if

- condition worsens
- redness is present
- irritation develops
- symptoms persist for more than 7 days or clear up and occur again within a few days
- you experience signs of skin injury, such as pain, swelling, or blistering where the product was applied

If pregnant or breast-feeding,

ask a health professional before use.

Keep out of reach of children and pets.

If swallowed, get medical help or contact a Poison Control Center right away.

Directions

adults and children over 12 years:

- apply a thin layer to affected area every 6 to 8 hours, not to exceed 3 applications in a 24 hour period
- AFTER APPLYING, WASH HANDS WITH SOAP AND WATER

children 12 years or younger: ask a doctor

Inactive ingredients

acrylates/C10-30 alkyl acrylate crosspolymer, aloe barbadensis leaf juice, aminomethyl propanol, cetearyl alcohol(and)dicetyl phosphate(and)ceteth-10 phosphate, cyclopentasiloxane, dimethicone, dimethicone/vinyl dimethicone crosspolymer, disodium EDTA, ethylhexylglycerin, glyceryl stearate, hydroxyethyl acrylate / sodium acryloyldimethyl taurate copolymer, isohexadecane, phenoxyethanol, SD alcohol 40 (15%), steareth-21, water

PRINCIPAL DISPLAY PANEL

SOUNDBODY
Lidocaine
Plus Menthol
Pain Relieving Cream